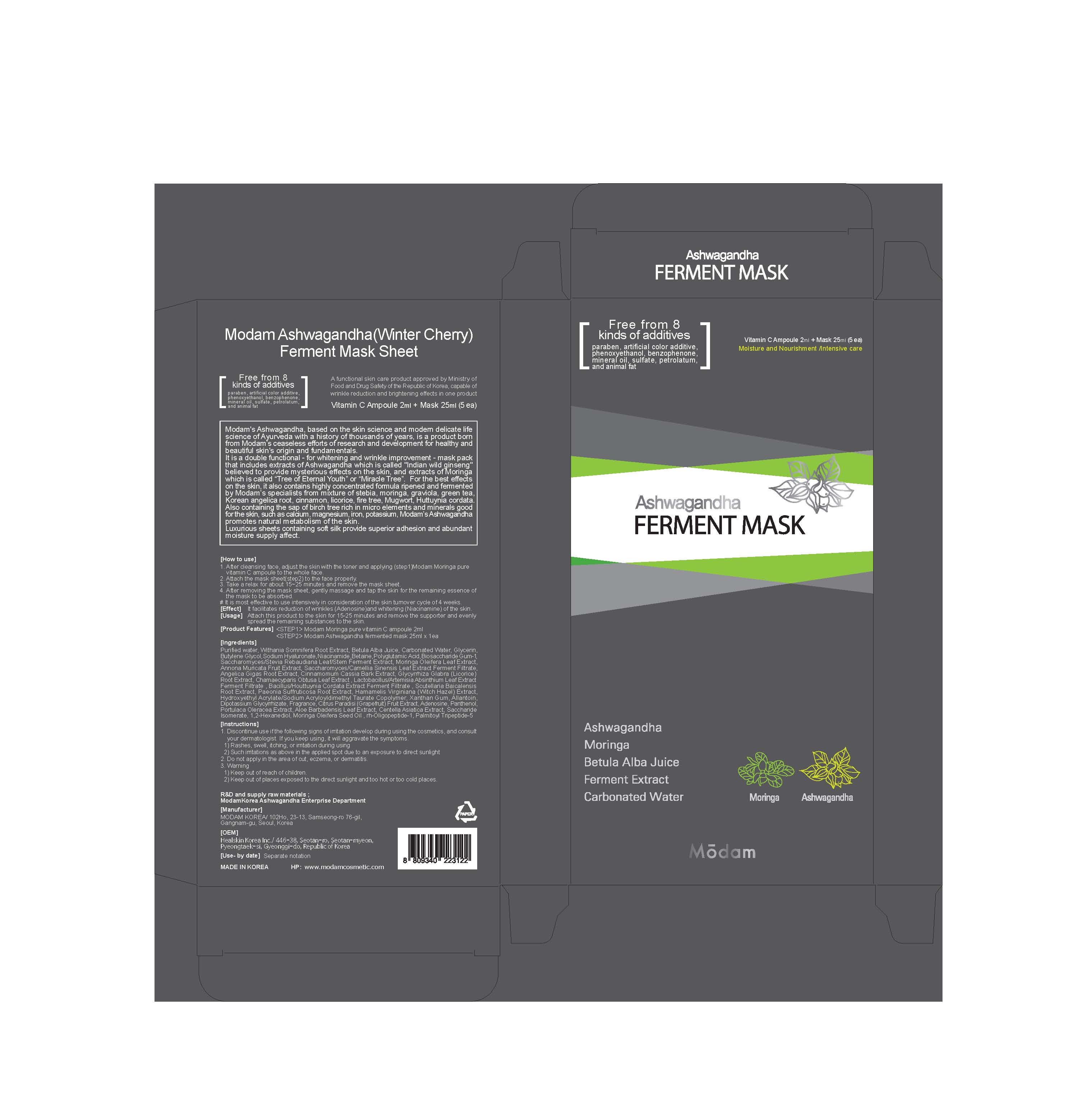 DRUG LABEL: Ashwagandha Ferment Mask
NDC: 72540-004 | Form: LIQUID
Manufacturer: MODAM KOREA
Category: otc | Type: HUMAN OTC DRUG LABEL
Date: 20190508

ACTIVE INGREDIENTS: GLYCERIN 1.131 g/25 mL; Allantoin 0.025 g/25 mL
INACTIVE INGREDIENTS: Water; Niacinamide; Propylene Glycol; Butylene Glycol; Chlorphenesin; Moringa Oleifera Seed Oil; Cetyl Ethylhexanoate; Phenoxyethanol; Squalane; Propolis Wax; Caprylyl Glycol; 1,2-Hexanediol; PEG-60 Hydrogenated Castor Oil; Ethylhexylglycerin

ACTIVE INGREDIENT

Glycerin (4.525%) - Skin Protectact

Allantoin (0.1%) - Skin Protectact

INACTIVE INGREDIENT

Water, Niacinamide, Propylene Glycol, Withania Somnifera Root Extract, Morus Bombycis Stem Extract, Butylene Glycol, Hydroxyethylcellulose, Aristoflex AVC, Chlorphenesin, Polyoxyethylene Hydrogenated Castor Oil, Aloe barbadensis Leaf Extract, Moringa Oleifera Seed Oil, Sodium Hyaluronate, Cetyl Ethylhexanoate, Moringa Pterygosperma Seed Extract, Adenosin, Polydimethylsiloxane, Phenoxyethanol, Squalane, Camellia Sinensis Leaf Extract, Coptis Chinensis Root Extract, Glycyrrhiza Glabra (Licorice) Root Extract, Schizandra Chinensis Fruit Extract, Zingiber Officinale (Ginger) Root Extract, Fragrance, Propolis Wax, Codonopsis Lanceolata Root Extract, Ficus Carica (Fig) Fruit Extract, Punica Granatum Fruit Extract, Caprylyl Glycol, 1,2-Hexanediol, Ethyl Hexanediol, Tert-Butanol, Particulate Not Otherwise Regulated (PNOR), Centella Asiatica Extract, PEG-60 Hydrogenated Castor Oil, Ethylhexylglycerin

PURPOSE

Skin Protectact

WARNINGS

1. Discontinue use if the following signs of irritation develop during using the cosmetics, and consult your dermatologist. If you keep using, it will aggravate the symptoms.
1) Rashes, swell, itching, or irritation during using
2) Such irritations as above in the applied spot due to an exposure to direct sunlight

2. Do not apply in the area of cut, eczema, or dermatitis.

3. Warning
1) Keep out of reach of children.
2) Keep out of places exposed to the direct sunlight and too hot or too cold places.

INDICATIONS & USAGE

[How to use]

1. After cleansing face, adjust the skin with the toner and applying (step1)Modam Moringa pure
vitamin C ampoule to the whole face.
2. Attach the mask sheet(step2) to the face properly.
3. Take a relax for about 15~25 minutes and remove the mask sheet.
4. After removing the mask sheet, gently massage and tap the skin for the remaining essence of the mask to be absorbed.

# It is most effective to use intensively in consideration of the skin turnover cycle of 4 weeks.

DOSAGE & ADMINISTRATION

Attach this product to the skin for 15-25 minutes and remove the supporter and evenly spread the remaining substances to the skin.